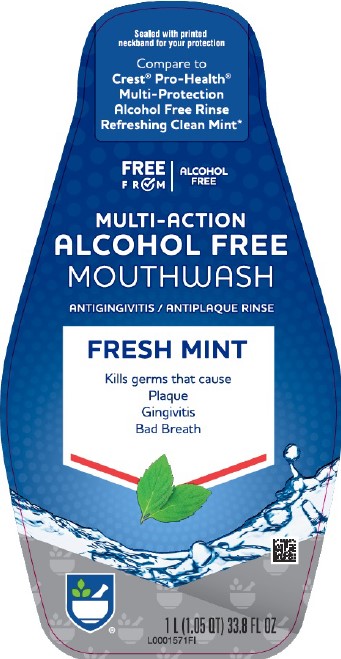 DRUG LABEL: Alcohol Free Antiseptic
NDC: 11822-5761 | Form: MOUTHWASH
Manufacturer: Rite Aid Corporation
Category: otc | Type: HUMAN OTC DRUG LABEL
Date: 20260130

ACTIVE INGREDIENTS: CETYLPYRIDINIUM CHLORIDE 0.7 mg/1 mL
INACTIVE INGREDIENTS: WATER; GLYCERIN; MENTHOL, UNSPECIFIED FORM; POLOXAMER 407; SACCHARIN SODIUM; PROPYLENE GLYCOL; SODIUM BENZOATE; SUCRALOSE; BENZOIC ACID; FD&C BLUE NO. 1

Rite Aid 299.006/299AK-AM
Multi Action Alcohol Free Antiseptic Rinse w/CPC

Claims

MULTI-ACTION

ALCOHOL FREE

MOUTHWASH

ANTIGINGIVITIS/ANTIPLAQUE RINSE

For better oral hygiene and fresher breath

Active ingredient

Cetylpyridinium chloride 0.07%

Purpose

Antigingivitis, Antiplaque

Use

helps control plaque {bacteria} that leads to gingivitis

Warnings

for this product

Stop use and ask a dentist if

- gingivitis, bleeding, or redness persists for more than 2 weeks
- you have painful or swollen gums, pus from the gum line, loose teeth or increased spacing between the teeth. These may be signs of symptoms of periodontitis, a serious form of gum disease.

Keep out of reach of children under 6 years of age

If more than used for rinsing is accidentally swallowed, get medical help or contact a Poison Control Center right away.

Directions

- adults and children 6 years & older: rinse for 30 seconds with 20 mL (4 teaspoonfuls) twice a day
- do not swallow
- children 6 years to under 12 years of age: supervise use
- when used after brushing, rinse mouth with water first
- children under 6 years of age: do not use

Other information

- this rinse is not intended to replace brushing or flossing

Inactive ingredients

water, glycerin, flavor, menthol, poloxamer 407, sodium saccharin, propylene glycol, sodium benzoate, sucralose, benzoic acid, blue 1

Disclaimer

This rinse may cause temporary staining to the surface of teeth. This is not harmful, and adequate brushing may prevent its occurrence.

*This product is not manufactured or distributed by Procter & Gamble, distributor of Crest ® Pro-Health ® Multi-Protection Alcohol Free Rinse – Refreshing Clean Mint.

Disclaimer

DISTRIBUTED BY:

RITE AID,

200 NEWBERRY COMMONS

ETTERS, PA 17319

www.riteaid.com

MADE IN THE US WITH US AND FOREIGN COMPONENTS

SATISFACTION GUARANTEE: If you're not satisfied, we'll happily refund your money.

Principal display panel

Sealed with printed neckband for your protection

Compare to Crest ® Pro-Health ® Multi-Protection Alcohol Free Rinse Refreshing Clean Mint*

FREE FROM

ALCOHOL FREE

MULTI-ACTION

ALCOHOL FREE

MOUTHWASH

ANTIGINGIVITIS/ANTIPLAQUE RINSE

FRESH MINT

Kills germs that cause

Plaque

Gingivitis

Bad Breath

1L (1.05 QT) 33.8 FL OZ